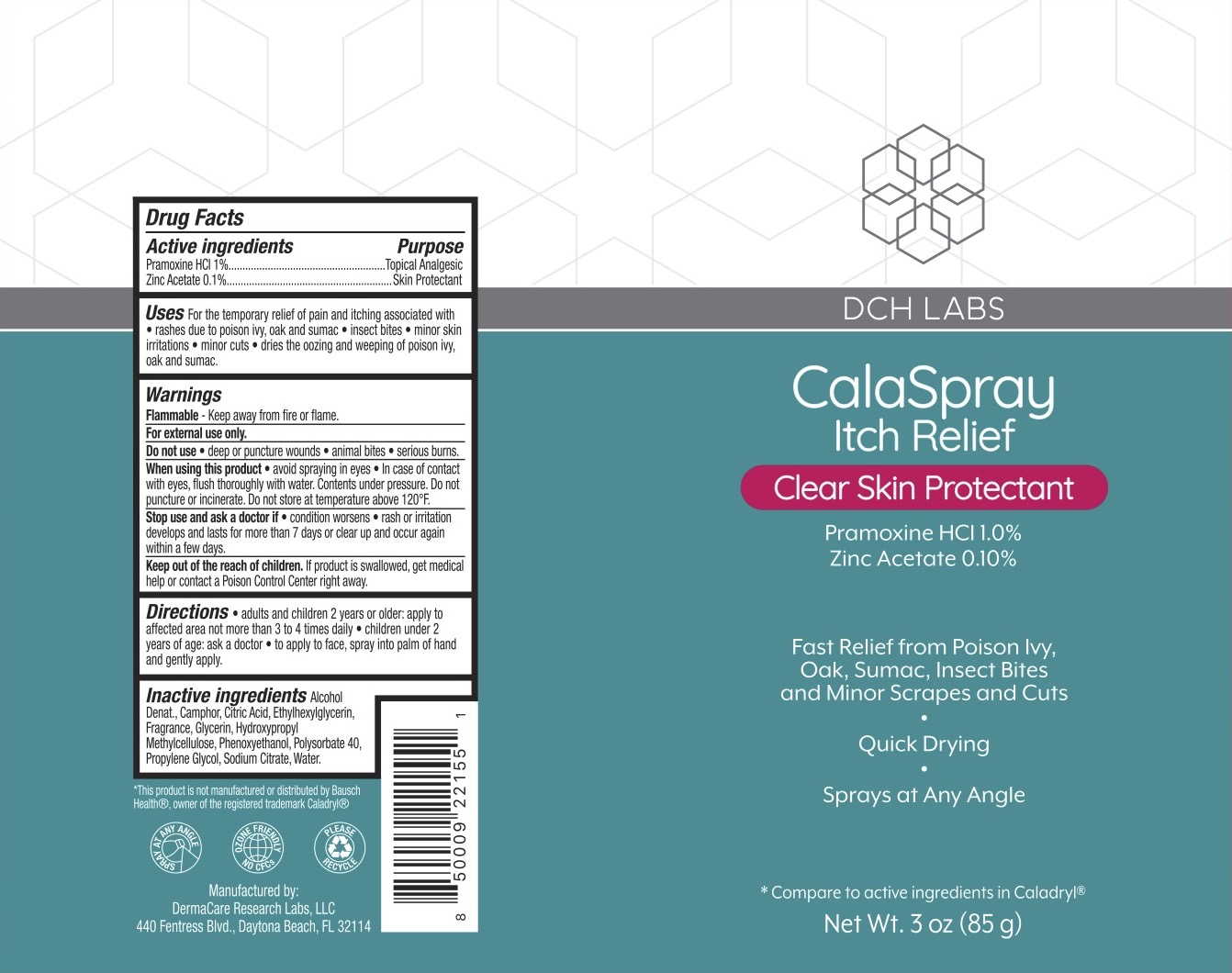 DRUG LABEL: DCH Calaspray Itch Relief
NDC: 72839-013 | Form: SPRAY
Manufacturer: Derma Care Research Labs, LLC
Category: otc | Type: HUMAN OTC DRUG LABEL
Date: 20241219

ACTIVE INGREDIENTS: PRAMOXINE HYDROCHLORIDE 1 g/100 g; ZINC ACETATE 0.1 g/100 g
INACTIVE INGREDIENTS: CITRIC ACID MONOHYDRATE; ETHYLHEXYLGLYCERIN; HYPROMELLOSES; CAMPHOR (SYNTHETIC); ALCOHOL; SODIUM CITRATE; GLYCERIN; WATER; POLYSORBATE 40; PROPYLENE GLYCOL; PHENOXYETHANOL

DCH Calaspray Itch Relief Spray, Pramoxine HCl 1%, Zinc Acetate 0.1%

ACTIVE INGREDIENT

Pramoxine HCl 2%, Zinc Acetate 0.1%

PURPOSE

Topical Analgesic, Skin Protectant

INDICATIONS AND USAGE

For the temporary relief of pain and itching associated with insect bites, minor burns, sunburn, minor cuts, scrapes, minor skin irritations, and rashes due to poison ivy, oak, and sumac. Dries the oozing and weeping of poison ivy, oak, and sumac.

WARNINGS

For external use only. Flammable--Keep away from fire or flame. Do not use on deep or puncture wounds, animal bites, or serious burns. When using this product avoid contact with eyes. In case of contact with eyes, flush thoroughly with water. Contents under pressure. Do not puncture or incinerate. Do not store at temperature above 120F. . Stop use and ask a doctor if condition worsens, if symptoms persist for more than 7 days or clear up and occur again within a few days.

KEEP OUT OF REACH OF CHILDREN

If swallowed, get medical help or contact a Poison Control Center right away.

DOSAGE AND ADMINISTRATION

Shake well before use. Adults and children 12 years of age and older, apply to the affected area not more than 3 to 4 times daily. Children under 12 years of age: ask a doctor. To apply to face, spray into palm of hand and gently apply.

INACTIVE INGREDIENT

Alcohol Denat., Camphor, Citric Acid, Ethylhexylglycerin, Fragrance, glycerin, Hydroxypropyl Methylcellulose, Phenoxyethanol, Polysorbate 40, Propylene Glycol, Sodium Citrate, Water.